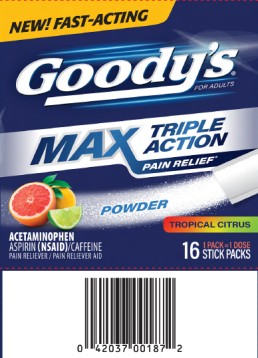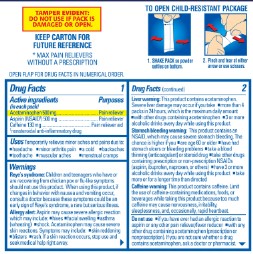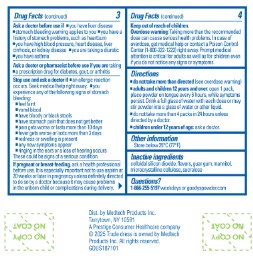 DRUG LABEL: GOODYS
NDC: 63029-668 | Form: POWDER
Manufacturer: Medtech Products Inc.
Category: otc | Type: HUMAN OTC DRUG LABEL
Date: 20260202

ACTIVE INGREDIENTS: ACETAMINOPHEN 500 mg/1 1; ASPIRIN 500 mg/1 1; CAFFEINE 130 mg/1 1
INACTIVE INGREDIENTS: SILICON DIOXIDE; GUAR GUM; MANNITOL; MICROCRYSTALLINE CELLULOSE; SUCRALOSE

Goodys Max Relief Tropical Citrus

GOODY’S

----------

Drug Facts

Active ingredients (in each powder)

Acetaminophen 500 mg

Aspirin (NSAID*) 500 mg

Caffeine 130 mg

*nonsteroidal anti-inflammatory drug

Purpose

Pain reliever

Pain reliever

Pain reliever aid

Uses

Temporarily relieves minor aches and pains due to:

- headache
- minor arthritis pain
- a cold
- backaches
- toothache
- muscular aches
- menstrual cramps

Warnings

Reye’s syndrome: Children and teenagers who have or are recovering from chicken pox or flu-like symptoms should not use this product. When using this product, if changes in behavior with nausea and vomiting occur, consult a doctor because these symptoms could be an early sign of Reye’s syndrome, a rare but serious illness.

Allergy alert: Aspirin may cause severe allergic reaction which may include:

- hives
- facial swelling
- asthma (wheezing)
- shock.

Acetaminophen may cause severe skin reactions. Symptoms may include:

- skin reddening
- blisters
- rash.

If a skin reaction occurs, stop use and seek medical help right away.

Liver warning: This product contains acetaminophen. Severe liver damage may occur if you take

- more than 4 packs in 24 hours, which is the maximum daily amount
- with other drugs containing acetaminophen
- 3 or more alcoholic drinks every day while using this product

Stomach bleeding warning: This product contains an NSAID, which may cause severe stomach bleeding. The chance is higher if you

- are age 60 or older
- have had stomach ulcers or bleeding problems
- take a blood thinning (anticoagulant) or steroid drug
- take other drugs containing prescription or non-prescription NSAIDs (aspirin, ibuprofen, naproxen, or others)
- have 3 or more alcoholic drinks every day while using this product
- take more or for a longer time than directed

Caffeine warning: This product contains caffeine. Limit the use of caffeine-containing medications, foods, or beverages while taking this product because too much caffeine may cause nervousness, irritability, sleeplessness, and, occasionally, rapid heartbeat.

Do not use

- if you have ever had an allergic reaction to aspirin or any other pain reliever/fever reducer
- with any other drug containing acetaminophen (prescription or nonprescription). If you are not sure whether a drug contains acetaminophen, ask a doctor or pharmacist.

Ask a doctor before use if

- you have liver disease
- stomach bleeding warning applies to you
- you have a history of stomach problems, such as heartburn
- you have high blood pressure, heart disease, liver cirrhosis, or kidney disease
- you are taking a diuretic
- you have asthma

Ask a doctor or pharmacist before use if you are taking

- a prescription drug for diabetes, gout, or arthritis

Stop use and ask a doctor if

- an allergic reaction occurs. Seek medical help right away.
- you experience any of the following signs of stomach bleeding:
  - feel faint
  - vomit blood
  - have bloody or black stools
  - have stomach pain that does not get better
  - pain gets worse or lasts more than 10 days
  - fever gets worse or lasts more than 3 days
  - redness or swelling is present
  - any new symptoms appear
  - ringing in the ears or a loss of hearing occurs

These could be signs of a serious condition.

If pregnant or breast-feeding,

ask a health professional before use. It is especially important not to use aspirin at 20 weeks or later in pregnancy unless definitely directed to do so by a doctor because it may cause problems in the unborn child or complications during delivery.

Keep out of reach of children.

Overdose warning: Taking more than the recommended dose can cause serious health problems. In case of overdose, get medical help or contact a Poison Control Center (1-800-222-1222) right away. Prompt medical attention is critical for adults as well as for children even if you do not notice any signs or symptoms.

Directions

- do not take more than directed (see overdose warning)
- adults and children 12 years and over: open 1 pack, place powder on tongue every 6 hours, while symptoms persist. Drink a full glass of water with each dose or may stir powder into a glass of water or other liquid.
- do not take more than 4 packs in 24 hours unless directed by a doctor.
- children under 12 years of age: ask a doctor.

Other information

Store below 25°C (77°F)

Inactive ingredients

colloidal silicon dioxide, flavors, guar gum, mannitol, microcrystalline cellulose, sucralose

Questions?

1-866-255-5197 weekdays or goodyspowder.com

Principal Display Panel

Goody’s® for adults

MAX PAIN RELIEF *

TRIPLE ACTION

POWDER

ACETAMINOPHEN

ASPIRIN (NSAID) / CAFFEINE

PAIN RELIEVER / PAIN RELIEVER AID

TROPICAL CITRUS

16 STICK PACKS

1 PACK = 1 DOSE